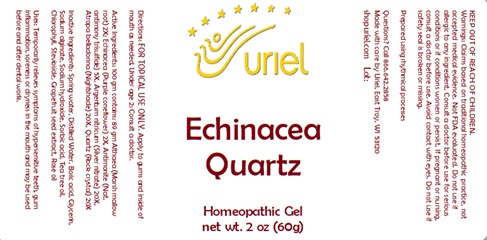 DRUG LABEL: Echinacea Quartz
NDC: 48951-4172 | Form: GEL
Manufacturer: Uriel Pharmacy, Inc.
Category: homeopathic | Type: HUMAN OTC DRUG LABEL
Date: 20241122

ACTIVE INGREDIENTS: SILVER 20 [hp_X]/1 g; ECHINACEA, UNSPECIFIED 2 [hp_X]/1 g; ANTIMONY TRISULFIDE 5 [hp_X]/1 g; ATROPA BELLADONNA 20 [hp_X]/1 g; SILICON DIOXIDE 20 [hp_X]/1 g; ALTHAEA OFFICINALIS ROOT 2 [hp_X]/1 g
INACTIVE INGREDIENTS: GLYCERIN; SODIUM ALGINATE; TEA TREE OIL; SORBIC ACID; CITRUS PARADISI SEED; STEVIOSIDE; WATER; BORIC ACID; SODIUM HYDROXIDE; ROSE OIL; CHLOROPHYLL

Echinacea Quartz

INDICATIONS AND USAGE

Directions: FOR TOPICAL USE ONLY.

DOSAGE AND ADMINISTRATION

Apply to gums and inside of mouth as needed. Under age 2: Consult a doctor.

ACTIVE INGREDIENT

Active Ingredients: 100 gm contains: 89 gm Althaea (Marsh mallow root) 2X; Echinacea (Purple coneflower) 2X, Antimonite (Nat. antimony trisulfide) 5X, Argentum nitricum (Silver nitrate) 20X, Atropa belladonna (Nightshade) 20X, Quartz (Rock crystal) 20X

INACTIVE INGREDIENT

Inactive Ingredients: Spring water, Distilled water, Boric acid, Glycerin, Sodium alginate, Sodium hydroxide, Sorbic acid, Tea tree oil, Chlorophyll, Stevioside, Grapefruit seed extract, Rose oil

Prepared using rhythmical processes.

PURPOSE

Uses: Temporarily relieves symptoms of hypersensitive teeth, gum inflammation, soreness or dryness in the mouth and may be used before and after dental work.

KEEP OUT OF REACH OF CHILDREN.

Warnings:
Claims based on traditional homeopathic practice, not accepted medical evidence. Not FDA evaluated. Do not use if allergic to any ingredient. Consult a doctor before use for serious conditions or if conditions worsen or persist. If pregnant or nursing, consult a doctor before use. Avoid contact with eyes. Do not use if safety seal is broken or missing.

Questions? Call 866.642.2858
Made with care by Uriel, East Troy, WI 53120
shopuriel.com